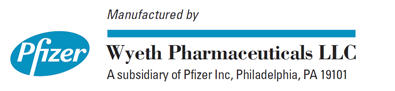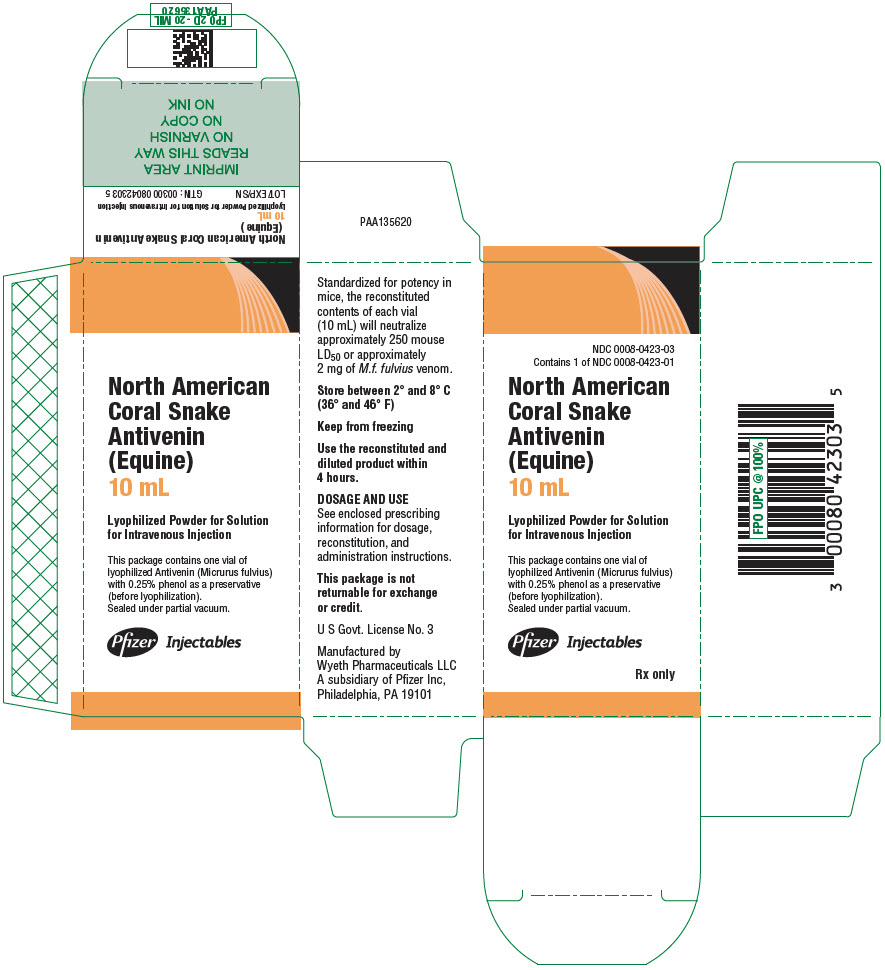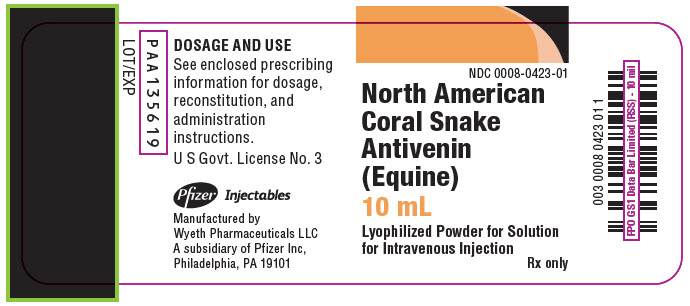 DRUG LABEL: North American Coral Snake Antivenin (Equine)
NDC: 0008-0423 | Form: INJECTION, POWDER, FOR SOLUTION
Manufacturer: Wyeth Pharmaceuticals LLC, a subsidiary of Pfizer Inc.
Category: prescription | Type: HUMAN PRESCRIPTION DRUG LABEL
Date: 20221122

ACTIVE INGREDIENTS: CORAL SNAKE (MICRURUS FULVIUS) IMMUNE GLOBULIN ANTIVENIN (EQUINE) 250 [arb'U]/10 mL
INACTIVE INGREDIENTS: PHENOL; THIMEROSAL

HIGHLIGHTS OF PRESCRIBING INFORMATION

These highlights do not include all the information needed to use North American Coral Snake Antivenin (Equine) safely and effectively. See full prescribing information for North American Coral Snake Antivenin (Equine).
North American Coral Snake Antivenin (Equine)
Lyophilized Powder for Solution for Intravenous Injection
Initial U.S. Approval: 1967

1 INDICATIONS AND USAGE

North American Coral Snake Antivenin (Equine) is a horse-derived antivenin indicated for the treatment of envenomation caused by North American coral snakes - Micrurus. (1)

2 DOSAGE AND ADMINISTRATION

For intravenous use only.

- In adults and adolescents, the dose may vary from 3 to 5 vials, depending on the response to treatment. (2.1)
- In small children, the dose may be decreased, depending on the response to treatment. (2.1)
- Contents of each reconstituted vial can neutralize approximately 250 mouse (Lethal Dose) LD50 or approximately 2 mg of M. fulvius venom. (2.1)
- Infuse the first 1 or 2 mL over a 3- to 5-minute period, observing for allergic reaction. If tolerated, administer the rest of the dose at the rate that is comfortable for the patient based on body weight and general condition. Do not exceed 4 mL per minute for children. (2.2)

3 DOSAGE FORMS AND STRENGTHS

Lyophilized powder in single use vial for reconstitution for injection. (3)

4 CONTRAINDICATIONS

- Do not administer North American Coral Snake Antivenin (Equine) prophylactically to asymptomatic patients. (4)
- Do not use in patients with a known history of hypersensitivity to horse serum unless the benefits outweigh the risks and appropriate management for anaphylactic reactions is readily available. (4)

5 WARNINGS AND PRECAUTIONS

Patients sensitive to North American Coral Snake Antivenin (Equine) or horse serum may develop anaphylaxis. Prior to intravenous North American Coral Snake Antivenin (Equine) administration consider performing a proper skin test and modify therapy if indicated. (5.1)

6 ADVERSE REACTIONS

Adverse reactions may include anaphylaxis and serum sickness, vomiting, and abdominal pain. (6)

To report SUSPECTED ADVERSE REACTIONS, contact Pfizer, Inc. at 1-800-438-1985 or FDA at 1-800-FDA-1088 or www.fda.gov/medwatch.

FULL PRESCRIBING INFORMATION

1 INDICATIONS AND USAGE

North American Coral Snake Antivenin (Equine) is indicated only for the treatment of envenomation caused by bites of North American coral snakes - Micrurus (including the eastern and Texas varieties).

2 DOSAGE AND ADMINISTRATION

For intravenous use only.

2.1 Dose

- Contents of each reconstituted vial can neutralize approximately 250 mouse (Lethal Dose) LD50 or approximately 2 mg of Micrurus fulvius fulvius (M. f. fulvius) venom.
- In adults and adolescents, the dose may vary from 3 to 5 vials, depending on the response to treatment.
- In small children, the dose may be decreased, depending on the response to treatment.

2.2 Preparation and Administration

Preparation

- Pry off the small metal disc in the cap over the diaphragms of the vials of North American Coral Snake Antivenin (Equine) and remove cap from diluent vials.
- Swab the exposed surface of the rubber diaphragms of both vials with an appropriate germicide.
- Withdraw 10 mL diluent (Sterile Water for Injection, USP) using a sterile syringe and needle, and insert the needle through the stopper of the vacuum-containing vial of North American Coral Snake Antivenin (Equine).
  - The vacuum in the North American Coral Snake Antivenin (Equine) vial will pull the diluent out of the syringe into the vial. Allow room air to be pulled into the North American Coral Snake Antivenin (Equine) vial until all vacuum is released.
  - Point the needle at the center of the lyophilized pellet of North American Coral Snake Antivenin (Equine) so that the diluent stream will wet the pellet.
- Reconstitute by swirling, not by shaking, for 1 minute, at 5-minute intervals until you observe complete dissolution of the lyophilized North American Coral Snake Antivenin (Equine). Complete reconstitution usually requires at least 30 minutes.

Administration

- Parenteral drug products should be inspected visually for particulate matter and discoloration prior to administration, whenever solution and container permit.
- Start an intravenous infusion of 250 to 500 mL of Sodium Chloride Injection, USP.
- Determine whether the patient has hypersensitivity to horse-serum in order to evaluate treatment decisions, and to prepare for treatment of anaphylaxis if it occurs [see Warnings and Precautions (5.1)].
- After reconstitution of the lyophilized North American Coral Snake Antivenin (Equine) administer the contents of 3 to 5 vials (30 to 50 mL) intravenously by slow injection directly into the intravenous tubing or the reservoir bottle of the intravenous solution. If added to reservoir bottle, mix by gentle swirling – do not shake.
- Administer the first 1 or 2 mL over a 3- to 5-minute period with careful observation of the patient for evidence of an allergic reaction. If no signs or symptoms of anaphylaxis appear, continue the injection or intravenous infusion.
- Adjust the infusion rate by the severity of signs and symptoms of envenomation and tolerance of North American Coral Snake Antivenin (Equine). Administer at the maximum safe rate for intravenous fluids, based on body weight and general condition of the patient.
  - For adults, if given by intravenous infusion to a previously healthy adult, allow 250 or 500 mL to run in within 30 minutes;
  - For small children, allow the first 100 mL to run in rapidly but then decrease to a rate not to exceed 4 mL per minute. Response to treatment may be rapid and dramatic.
- Observe the patient carefully and administer additional North American Coral Snake Antivenin (Equine) intravenously as required.

3 DOSAGE FORMS AND STRENGTHS

Each package contains one single use vial with lyophilized North American Coral Snake Antivenin (Equine) for dilution with 10 mL of diluent (Sterile Water for Injection, USP). Contents of each reconstituted vial can neutralize approximately 250 mouse (Lethal Dose) LD50 or approximately 2 mg of M. f. fulvius venom.

4 CONTRAINDICATIONS

- Do not administer North American Coral Snake Antivenin (Equine) prophylactically to asymptomatic patients.^1
- Do not administer North American Coral Snake Antivenin (Equine) to patients with a known history of hypersensitivity to horse serum unless the benefits outweigh the risks and appropriate management for anaphylactic reactions is readily available.

5 WARNINGS AND PRECAUTIONS

5.1 Hypersensitivity Reactions

Patients sensitive to North American Coral Snake Antivenin (Equine) or horse serum may develop anaphylaxis. Prior to intravenous North American Coral Snake Antivenin (Equine) administration, consider performing a proper skin test and modify therapy if indicated.

Consider the following precautions to manage hypersensitivity reactions:

- Emergency medical care (e.g., epinephrine, intravenous antihistamines and/or albuterol) should be readily available.
- Carefully monitor patients for signs and symptoms of an acute allergic reaction (e.g., urticaria, pruritus, erythema, angioedema, bronchospasm with wheezing or cough, stridor, laryngeal edema, hypotension, tachycardia).
- Follow-up all patients for signs and symptoms of delayed allergic reactions or serum sickness (e.g., rash, fever, myalgia, arthralgia).

Patients who receive a course of treatment with a foreign protein such as North American Coral Snake Antivenin (Equine) may become sensitized to it. Therefore, use caution when administering a repeat course of treatment with North American Coral Snake Antivenin (Equine) for a subsequent envenomation episode.

6 ADVERSE REACTIONS

The most common adverse reactions observed after treatment with North American Coral Snake Antivenin (Equine) were anaphylaxis and serum sickness, vomiting, and abdominal pain. Because these reactions were reported voluntarily from a population of uncertain size, it is not always possible to estimate their frequency reliably or to establish a causal relationship to drug exposure.

8 USE IN SPECIFIC POPULATIONS

8.1 Pregnancy

Risk Summary

There are no available human data that establish developmental toxicity related to the use of North American Coral Snake Antivenin (Equine). There are no available animal data informing the North American Coral Snake Antivenin (Equine)-associated risk. North American Coral Snake Antivenin (Equine) should be given to a pregnant woman only if clearly required. In the US general population, the background risk of major birth defects is 2–4% and of miscarriage is 15–20% in clinically recognized pregnancies.

8.2 Lactation

Risk Summary

Lactation studies have not been conducted with North American Coral Snake Antivenin (Equine). It is not known whether North American Coral Snake Antivenin (Equine) is excreted in human milk. North American Coral Snake Antivenin (Equine) should be administered to lactating women only if clearly indicated. The developmental and health benefits of breastfeeding should be considered along with the mother's clinical need for North American Coral Snake Antivenin (Equine) and any potential adverse effects on the breastfed child from North American Coral Snake Antivenin (Equine) or from the underlying maternal condition.

8.4 Pediatric Use

Controlled clinical studies of safety and effectiveness in pediatric patients have not been conducted.

Potential cases of Coral Snake envenomation and subsequent treatment with North American Coral Snake Antivenin (Equine) have been reported in pediatric patients;^2 adverse reactions included anaphylaxis (wheezing) requiring treatment with epinephrine, vomiting, and abdominal pain.

8.5 Geriatric Use

Specific studies in elderly patients have not been conducted.

11 DESCRIPTION

North American Coral Snake Antivenin (Equine) is a sterile lyophilized powder for solution for injection containing serum globulins obtained by fractionating blood from healthy horses that have been immunized with eastern coral snake (Micrurus fulvius fulvius) venom. Prior to lyophilization, the product contains 0.25% phenol.

12 CLINICAL PHARMACOLOGY

12.1 Mechanism of Action

North American Coral Snake Antivenin (Equine) specifically binds to and neutralizes coral snake venom.

12.2 Pharmacodynamics

North American Coral Snake Antivenin (Equine) is standardized for potency in mice in terms of its LD50 neutralizing capacity per milliliter as determined by intravenous injection of a graded series of mixtures of North American Coral Snake Antivenin (Equine) with M. f. fulvius venom. Based on this assay system, the reconstituted contents of each vial (10 mL) will neutralize approximately 250 mouse LD50 or approximately 2 mg of M.f. fulvius venom.

The results of cross-neutralization tests indicate that North American Coral Snake Antivenin (Equine) will neutralize the venom of M. fulvius tenere (Texas coral snake) but will not neutralize the venom of Micruroides euryxanthus (Arizona or Sonoran coral snake).

14 CLINICAL STUDIES

There have been no well-controlled clinical studies of the use of North American Coral Snake Antivenin (Equine) in patients experiencing envenomation by the Eastern Coral Snake, however a retrospective analysis^3 has been published of 387 coral snake exposures treated in a healthcare facility in Florida between 1998 and 2010, including 252 patients who were treated with North American Coral Snake Antivenin (Equine). Patients were managed according to different treatment strategies: (a) asymptomatic at ED arrival and treated empirically (n=134); (b) asymptomatic at ED arrival, but treatment withheld until symptoms appeared (n=106; 6 of the 106 received North American Coral Snake Antivenin (Equine) at some point; the remainder were never treated); (c) symptomatic at ED arrival and treated with North American Coral Snake Antivenin (Equine) (n=112); and (d) symptomatic at ED arrival but not treated with North American Coral Snake Antivenin (Equine) (n=35). The average number of vials administered to treated patients was 3.75 (range 1 – 20 vials); the 17 patients who received repeat treatment were administered 8.3 vials, on average. There was no reported usage of foreign antivenom or acetylcholinesterase inhibitors in this case series. The 387 patients were assessed for clinical outcomes, as shown in Table 1. Outcomes codes range from full recovery with no residual effects ("No Effect") to less than full recovery with significant residual effects ("Major"). Empiric treatment of asymptomatic patients resulted in more 'moderate' and 'major' outcomes compared to withholding treatment until symptoms appeared (p<.001), however, the patients were not randomized and selection biases could have affected this result.

Table 1 – Outcome by Treatment Strategy
Treatment Strategy | Empiric (N = 134) | Withhold (N = 106) | Symptomatic with AV (N = 112) | Symptomatic without AV (N = 35)
Primary outcome
Endotracheal intubation (%) | 3 (2.2) | 1 (0.94) | 7 (6.25) | 0 (0)
Secondary outcomes
Days intubated Avg. (SD) | 5.67 (2.89) | 24 (N/A) | 8 (6.22) | 0 (0)
ICU admission (%) [p < 0.01 between empiric and withhold strategies.] | 97 (72.39) | 49 (46.23) | 90 (80.36) | 9 (25.71)
ICU LOS Avg.(SD) | 1.5 (1.18) | 1.73 (3.28) | 2.25 (3.35) | 1.3 (0.5)
Total LOS Avg.(SD) | 1.58 (1.56) | 1.17 (2.94) | 2.47 (3.68) | 0.94 (0.85)
Antivenom ADR (%) | 26 (19.4) | 0 (0) | 20 (17.86) | 0 (0)
Outcome code %
No Effect | 4.76 | 29.29 | 0 | 0
Minor | 71.43 | 56.57 | 34.23 | 63.64
Moderate | 20.63 | 13.13 | 54.05 | 36.36
Major | 3.17 | 1.01 | 11.71 | 0
ADR, adverse drug reaction; AV, antivenom; Avg, average; LOS, length of stay; ICU, intensive care unit.

Adverse reactions associated with North American Coral Snake Antivenin (Equine) administration were documented in 46 (18.25%) cases. The most common adverse reactions were hives, rash and/or welts (12%); itching (9%); shortness of breath (8%); hypotension (2%) and angioedema (1%). Antihistamines were administered to 46 patients, corticosteroids to 40, and epinephrine to 10 cases to treat these adverse reactions.

15 REFERENCES

1. Bowden, C and Krenzelok, E: Clinical applications of commonly used contemporary antidotes, a US perspective. Drug Safety 1997; 16(1):9-47.
2. Sasaki, J et al: Coral snake bites and envenomation in children, A case series. Ped Emerg Care 2014; 30(4):262-5.
3. Wood A, Schauben J, Thundiyil J, et al. Review of Eastern coral snake (Micrurus fulvius fulvius) exposures managed by the Florida Poison Information Center Network: 1998-2010. Clin Toxicol 2013; 51(8):783-8.

16 HOW SUPPLIED/STORAGE AND HANDLING

North American Coral Snake Antivenin (Equine) is supplied as a sterile lyophilized powder in single use vial (NDC 0008-0423-01) in a carton (NDC 0008-0423-03).

STORAGE AND HANDLING

Store vials between 2 and 8°C (36 and 46° F). Do not freeze.

Use the reconstituted and diluted product within 4 hours.

17 PATIENT COUNSELING INFORMATION

Advise patients to contact the physician or emergency department immediately if they experience any signs and symptoms of delayed allergic reactions or serum sickness up to 14 days following hospital discharge. Symptoms include rash, pruritus, joint pain, arthralgia, fever, lymphadenopathy, and malaise.

U.S. Govt. License No. 3

This product's label may have been updated. For current full prescribing information, please visit www.pfizer.com.

LAB-0726-7.0

PRINCIPAL DISPLAY PANEL - 10 mL Vial Label

NDC 0008-0423-01

North American
Coral Snake
Antivenin
(Equine)
10 mL

Lyophilized Powder for Solution
for Intravenous Injection

Rx only

PRINCIPAL DISPLAY PANEL - 10 mL Vial Carton

NDC 0008-0423-03
Contains 1 of NDC 0008-0423-01

North American
Coral Snake
Antivenin
(Equine)
10 mL

Lyophilized Powder for Solution
for Intravenous Injection

This package contains one vial of
lyophilized Antivenin (Micrurus fulvius)
with 0.25% phenol as a preservative
(before lyophilization).
Sealed under partial vacuum.

Pfizer Injectables

Rx only